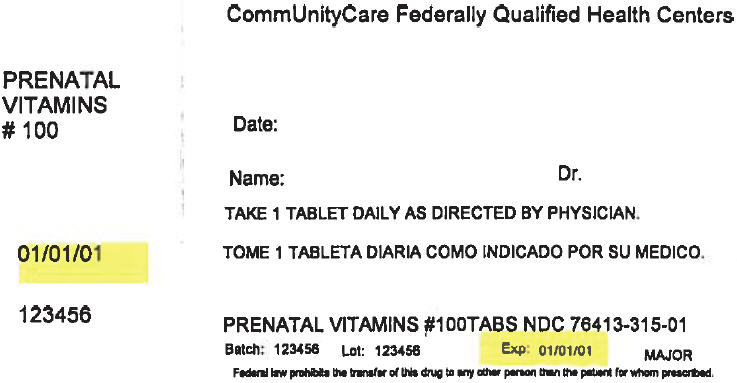 DRUG LABEL: Prenatal
NDC: 76413-315 | Form: TABLET
Manufacturer: Central Texas Community Health Centers
Category: other | Type: DIETARY SUPPLEMENT
Date: 20170915

ACTIVE INGREDIENTS: Vitamin A 4000 [iU]/1 1; Ascorbic Acid 100 mg/1 1; Cholecalciferol 400 [iU]/1 1; .Alpha.-Tocopherol 11 [iU]/1 1; Thiamine 1.5 mg/1 1; Riboflavin 1.7 mg/1 1; Niacin 18 mg/1 1; Pyridoxine 2.6 mg/1 1; Folic acid 0.8 mg/1 1; Cyanocobalamin 4 ug/1 1; Calcium 263 mg/1 1; Ferrous fumarate 27 mg/1 1; Zinc oxide 25 mg/1 1
INACTIVE INGREDIENTS: Microcrystalline cellulose; stearic acid; Hypromellose, Unspecified; croscarmellose sodium; Gelatin, Unspecified; acacia; maltodextrin; titanium dioxide; talc; triacetin; magnesium stearate; Anhydrous Dibasic Calcium Phosphate; mineral oil; sucrose; Silicon Dioxide; sodium ascorbate; FD&C Red NO. 40; FD&C Yellow NO. 6; Aluminum Oxide; Tocopherol; Sodium Benzoate; Sorbic acid; Tricalcium Phosphate; Butylated Hydroxytoluene; Ascorbyl Palmitate

Prenatal Tablets

STATEMENT OF IDENTITY

Supplement Facts
Serving Size: 1 Tablet
Amount Per Serving | % Daily Value [% Daily Value for Pregnant and Lactating Women]
Vitamin A (as Acetate and Beta Carotene) | 4000 I.U. | 50%
Vitamin C (as Ascorbic Acid) | 100 mg. | 167%
Vitamin D-3 (as Cholecalciferol) | 400 I.U. | 100%
Vitamin E (as dl-Alpha Tocopheryl Acetate) | 11 I.U. | 37%
Vitamin B-1 (as Thiamine Mononitrate) | 1.5 mg. | 88%
Vitamin B-2 (Riboflavin) | 1.7 mg. | 85%
Vitamin B-3 (as Niacinamide) | 18 mg. | 90%
Vitamin B-6 (as Pyridoxine HCl) | 2.6 mg. | 104%
Folic Acid | 0.8 mg. | 100%
Vitamin B-12 (as Cyanocobalamin) | 4 mcg. | 50%
Calcium (as Calcium Carbonate and Calcium Sulfate) | 263 mg. | 26%
Iron (as Ferrous Fumarate) | 27 mg. | 150%
Zinc (as Zinc Oxide) | 25 mg. | 167%

OTHER INGREDIENTS: Microcrystalline Cellulose, Stearic Acid, Hypromellose, Croscarmellose Sodium, Gelatin, Acacia, Maltodextrin, Titanium Dioxide, Talc, Triacetin, Starch, Magnesium Stearate, Dicalcium Phosphate, Mineral Oil, Sucrose, Silica, Sodium Ascorbate, Triglycerides, FD&C Red #40 Lake, FD&C Yellow #6 Lake, Tocopherols, Sodium Benzoate, Sorbic Acid, Tricalcium Phosphate, BHT and Ascorbyl Palmitate.

DIRECTIONS

For adults, take one (1) tablet daily, preferably with a meal. As a reminder, discuss the supplements and medications you take with your health care providers.

WARNING

If you are pregnant, nursing, taking any medications or planning any medical procedure, consult your doctor before use. Discontinue use and consult your doctor if any adverse reactions occur.

WARNING: Accidental overdose of iron-containing products is a leading cause of fatal poisoning in children under six. KEEP THIS PRODUCT OUT OF THE REACH OF CHILDREN. In case of accidental overdose, call a doctor or Poison Control Center immediately.

FREE OF

Yeast, wheat, milk or milk derivatives, soy, artificial flavor, sodium (less than 5 mg per serving).

HEALTH CLAIM

STORE AT ROOM TEMPERATURE AND AVOID EXCESSIVE HEAT. TAMPER RESISTANT: DO NOT USE IF SEAL UNDER CAP IS BROKEN OR MISSING.

HEALTH CLAIM

Distributed by: MAJOR® PHARMACEUTICALS
31778 Enterprise Drive, Livonia, MI 48150, USA
Questions or Comments? (800) 616-2471

M-29
Rev. 03/16
7434-03-16

PRINCIPAL DISPLAY PANEL - 100 Tablet Bottle Label

CommUnityCare Federally Qualified Health Centers

PRENATAL
VITAMINS
# 100

Date:

Name:
Dr.

TAKE 1 TABLET DAILY AS DIRECTED BY PHYSICIAN.

01/01/01

123456

PRENATAL VITAMINS #100TABS NDC 76413-315-01

Batch:
123456
Lot:
123456
Exp:
01/01/01

MAJOR

Federal law prohibits the transfer of this drug to any other person than the patient for whom prescribed.